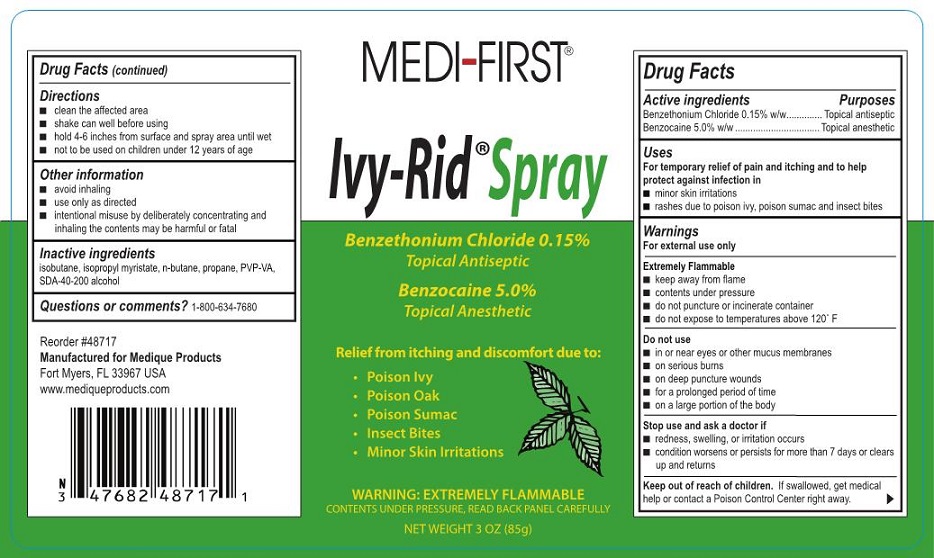 DRUG LABEL: Medi-first Ivy-Rid First Aid
NDC: 47682-487 | Form: AEROSOL, SPRAY
Manufacturer: Unifirst First Aid Corporation
Category: otc | Type: HUMAN OTC DRUG LABEL
Date: 20250908

ACTIVE INGREDIENTS: BENZOCAINE 4250 mg/85 g; BENZETHONIUM CHLORIDE 127.5 mg/85 g
INACTIVE INGREDIENTS: ISOPROPYL MYRISTATE; COPOVIDONE K25-31; ALCOHOL; BUTANE; PROPANE; ISOBUTANE

Medi-First Ivy-Rid Spray

Active ingredient

Benzocaine 5.0% w/w
Benzetonium Chloride 0.15% w/w

Purposes

Topical anesthetic
Topical antiseptic

Uses

For temporary relief of pain and itching and to help protect against infection in

- minor skin irritations
- rashes due to poison ivy, poison sumac and insect bites

Warnings

For external use only

Extremely Flammable

- keep away from flame
- contents under pressure
- do not puncture or incinerate container
- do not expose to temperatures above 120° F

Do not use

- in or near eyes or other mucous membranes
- in case of serious burns
- in deep puncture wounds
- for a prolonged period of time
- on large portions of the body

Keep out of the reach of children.

If swallowed, get medical help or contact a Poison Control Center right away.

Directions

- clean the affected area
- shake can well before using
- hold 4-6 inches from surface and spray area until wet
- for adult institutional use only
- not intended for use on children

Inactive Ingredients

isopropyl myristate, PVP-VA, SDA-400-200 alcohol, n-butane, isobutane

Medi-First Ivy Rid Spray Label

Medi-First®

Ivy-Rid® Spray

Benzethonium Chloride 0.15%
Topical Antiseptic

Benzocaine 5.0%\Topical Anesthetic

Relief from itching and discomfort due to:

- Poison Ivy
- Poison Oak
- Poison Sumac
- Insect Bites
- Minor Skin Irritations

WARNING: EXREMELY FLAMMABLE

Contents Under Pressure, Read Bacl Panel Carefully

Net Weight 3 OZ (85g)